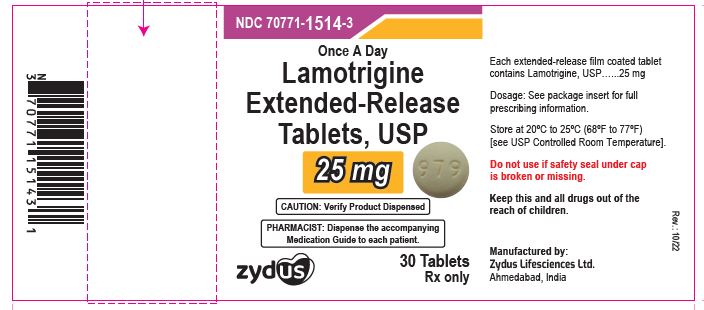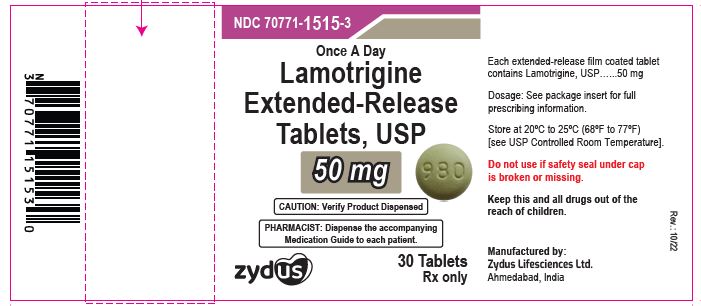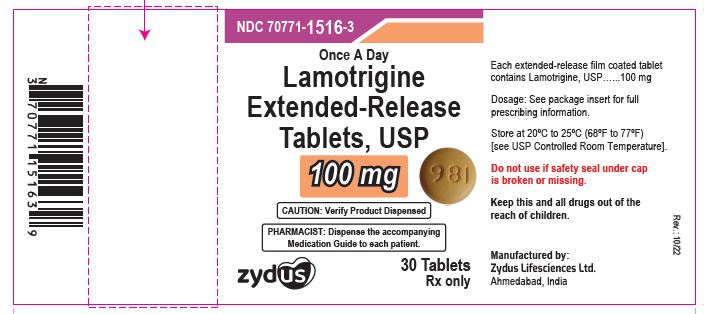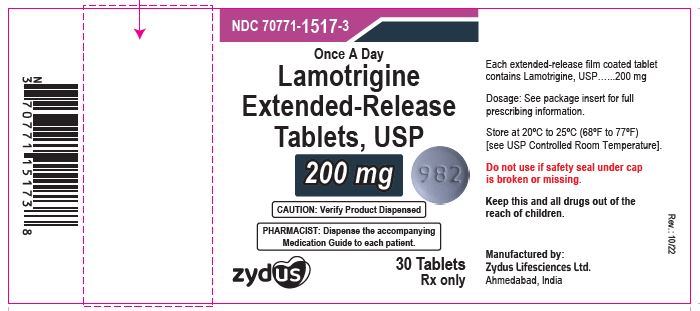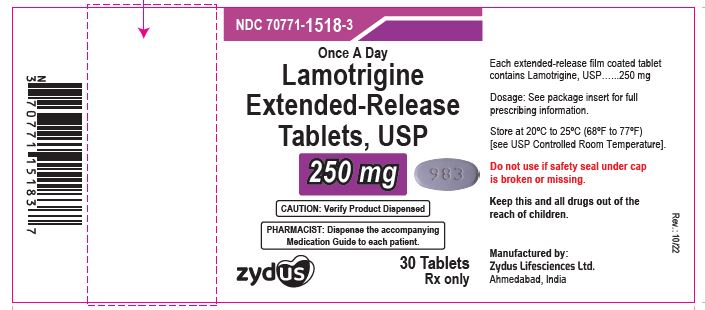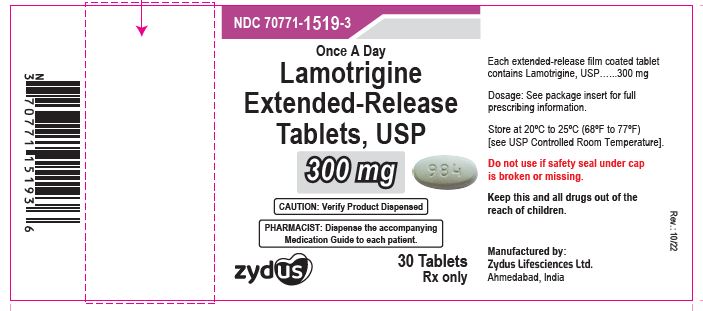 DRUG LABEL: Lamotrigine
NDC: 70771-1514 | Form: TABLET, EXTENDED RELEASE
Manufacturer: Zydus Lifesciences Limited
Category: prescription | Type: HUMAN PRESCRIPTION DRUG LABEL
Date: 20241130

ACTIVE INGREDIENTS: LAMOTRIGINE 25 mg/1 1
INACTIVE INGREDIENTS: D&C YELLOW NO. 10; FERRIC OXIDE RED; FERRIC OXIDE YELLOW; GLYCERYL MONOSTEARATE; HYPROMELLOSES; LACTOSE MONOHYDRATE; MAGNESIUM STEARATE; METHACRYLIC ACID AND ETHYL ACRYLATE COPOLYMER; POLYETHYLENE GLYCOL, UNSPECIFIED; POLYSORBATE 80; TRIETHYL CITRATE; TITANIUM DIOXIDE; WATER

LAMOTRIGINE Extended-release Tablets

PACKAGE LABEL.PRINCIPAL DISPLAY PANEL

NDC 70771-1514-3

Lamotrigine extended-release tablets, 25 mg

Rx only

30 tablets

NDC 70771-1515-3

Lamotrigine extended-release tablets, 50 mg

Rx only

30 tablets

NDC 70771-1516-3

Lamotrigine extended-release tablets, 100 mg

Rx only

30 tablets

NDC 70771-1517-3

Lamotrigine extended-release tablets, 200 mg

Rx only

30 tablets

NDC 70771-1518-3

Lamotrigine extended-release tablets, 250 mg

Rx only

30 tablets

NDC 70771-1519-3

Lamotrigine extended-release tablets, 300 mg

Rx only

30 tablets